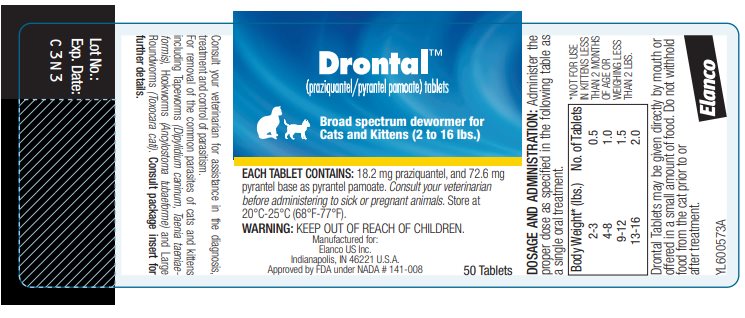 DRUG LABEL: Drontal
NDC: 58198-0034 | Form: TABLET
Manufacturer: Elanco US Inc.
Category: animal | Type: OTC ANIMAL DRUG LABEL
Date: 20260223

ACTIVE INGREDIENTS: PRAZIQUANTEL 18.2 mg/1 1; PYRANTEL PAMOATE 72.6 mg/1 1

Elanco™
Drontal™
(praziquantel/pyrantel pamoate)
Tablets
Broad Spectrum Dewormer
For Cats And Kittens

DESCRIPTION:

Drontal (praziquantel/pyrantel pamoate) Broad Spectrum Dewormer Tablets for Cats and Kittens are scored for easy breakage. Each tablet contains 18.2 mg praziquantel and 72.6 mg pyrantel base as pyrantel pamoate.

DIRECTIONS FOR USE:

Drontal (praziquantel/pyrantel pamoate) tablets will remove Tapeworms (Dipylidium caninum, Taenia taeniaeformis), Hookworms (Ancylostoma tubaeforme), and Large Roundworms (Toxocara cati) in cats and kittens.

The presence of tapeworms is indicated by the observance of tapeworm segments passed in the cat's feces. Tapeworm segments are white, pinkish-white or yellow-white in color and are similar in size and shape to flattened grains of rice. The segments are most frequently observed lying on a freshly passed stool. Segments may also be found on the hair around the anus of the animal or on the animal's bedding. Cats become infected with tapeworms after eating fleas or small mammals (rabbits, mice) which may be infected with tapeworm larvae.

Hookworms are small whitish or reddish-brown worms less than one inch in length that live in the intestinal tract and feed on blood. Cats can become infected with hookworms by swallowing infected larvae while grooming or when larvae from the environment burrow through the skin. Cats infected with hookworms may have poor physical condition, dull haircoat, and reduced body weight and diarrhea, sometimes with the presence of dark blood.

Large roundworms are white or yellow-white strands 2-7 inches in length (similar in size and color to smooth strings of spaghetti) that may be observed in the cat's vomit or feces. Cats become infected with large roundworms by swallowing infective eggs, particularly while grooming, or by ingestion of mice that may be infected with larval stages.

Large roundworms and hookworms pass eggs in the feces of the cat that can only be observed with the aid of a microscope.

The presence of these parasites should be confirmed through identification of parasite eggs in the feces.

Consult your veterinarian for assistance in the diagnosis, treatment and control of parasites.

Large roundworms and hookworms may be observed in the feces of the cat a day or so after the cat has been treated with Drontal Tablets. The majority of tapeworms, however, are digested and are not found in the feces after treatment.

DOSAGE AND ADMINISTRATION:

To assure proper dosage, weigh the cat prior to treatment. Select the number of whole or partial tablets needed for the cat from the following table.

Body Weight* (lbs.) | Number of Tablets
2 – 3 | ½
4 – 8 | 1
9 – 12 | 1 ½
13 – 16 | 2
*NOT FOR USE IN KITTENS LESS THAN TWO MONTHS OF AGE OR WEIGHING LESS THAN 2 LBS.

Drontal Tablets may be given directly by mouth or offered in a small amount of food. Do not withhold food from the cat prior to or after treatment.

EFFICACY:

A total of 93 cats with naturally acquired parasite infections were included in two well-controlled laboratory studies to establish the efficacy of Drontal Tablets. In addition, 85 cats and kittens of various sizes, ages and breeds were included in clinical field studies conducted at six veterinary clinics at different geographic locations throughout the United States. Data indicate 98% of the cats were completely cleared of parasite infections within 7 days of treatment. These studies demonstrated Drontal Tablets are safe and efficacious for the removal of the parasite species indicated on the label when used as directed.

SAFETY:

Cats treated with 10 times the highest recommended Drontal Tablet dosage during safety studies showed signs of vomition and salivation without other adverse effects. Eighty-three of 85 cats treated with the recommended dosages of Drontal Tablets in a clinical field study did not exhibit any drug related side effects. A temporary loss of appetite was reported for one cat and transient loose stools were observed in a second cat.

ADVERSE REACTIONS:

Post-Approval Experience: Although not all adverse reactions are reported, based on voluntary post-approval reporting, transient ataxia has been reported following the administration of Drontal Tablets for Cats and Kittens.

RETREATMENT:

Steps should be taken to prevent parasite infections, otherwise retreatment will be necessary.

Tapeworms transmitted by fleas will likely recur unless measures are taken to control fleas. Flea control procedures must include insecticide treatment of the cat's environment (i.e. bedding and resting areas) as well as direct treatment of the cat with topical solutions, dips, powders, sprays or other approved insecticides.

Roundworms and hookworms are controlled in cats by maintaining an environment free of infective eggs and larvae. Feces and soiled litter should be removed on a daily basis to prevent build-up of eggs and larvae in the environment.

Certain parasites such as tapeworms and large roundworms are transmitted to the cat after they eat infected rodents. Controlling the predatory habits of cats , i.e., catching and eating rodents, will prevent these parasite infections.

Cats maintained under conditions of constant exposure to parasite infections should have a follow-up fecal exam within 2 to 4 weeks after the first treatment.

If reinfection with tapeworms, hookworms or large roundworms occurs, treatment with Drontal Tablets may be repeated.

WARNING:

KEEP OUT OF REACH OF CHILDREN.

Consult your veterinarian before administering to sick or pregnant animals.

Questions/Comments?

For product questions or to report side effects, contact Elanco US Inc. at 1-888-545-5973.

For additional information about reporting side effects for animal drugs, contact FDA at 1-888-FDA-VETS or http://www.fda.gov/reportanimalae

STORAGE CONDITIONS:

Store at 20°C-25°C (68°F-77°F), excursions permitted between 15°C-30°C (59°F-86°F). Brief exposure to temperatures up to 40°C (104°F); however such exposure should be minimized.

HOW SUPPLIED:

Drontal Tablets are available in 50 tablet bottles.

– 50 tablets/bottle

Elanco™

Manufactured for:

Elanco US Inc.

Indianapolis, IN 46221 U.S.A.

Approved by FDA under NADA # 141-008

Drontal, Elanco and the diagonal bar logo are trademarks of Elanco or its affiliates.

© 2025 Elanco or its affiliates Revised: November 2025

PA600573X

Principal Display Panel – 50 Tablet Bottle Label

Drontal™

(praziquantel/pyrantel pamoate) tablets

Broad spectrum dewormer for
Cats and Kittens (2 to 16 lbs.)

EACH TABLET CONTAINS: 18.2 mg praziquantel, and 72.6 mg
pyrantel base as pyrantel pamoate. Consult your veterinarian
before administering to sick or pregnant animals. Store at
20°C-25°C (68°F-77°F).

WARNING: KEEP OUT OF REACH OF CHILDREN.

Manufactured for:

Elanco US Inc.

Indianapolis, IN 46221 U.S.A.

Approved by FDA under NADA # 141-008

50 Tablets